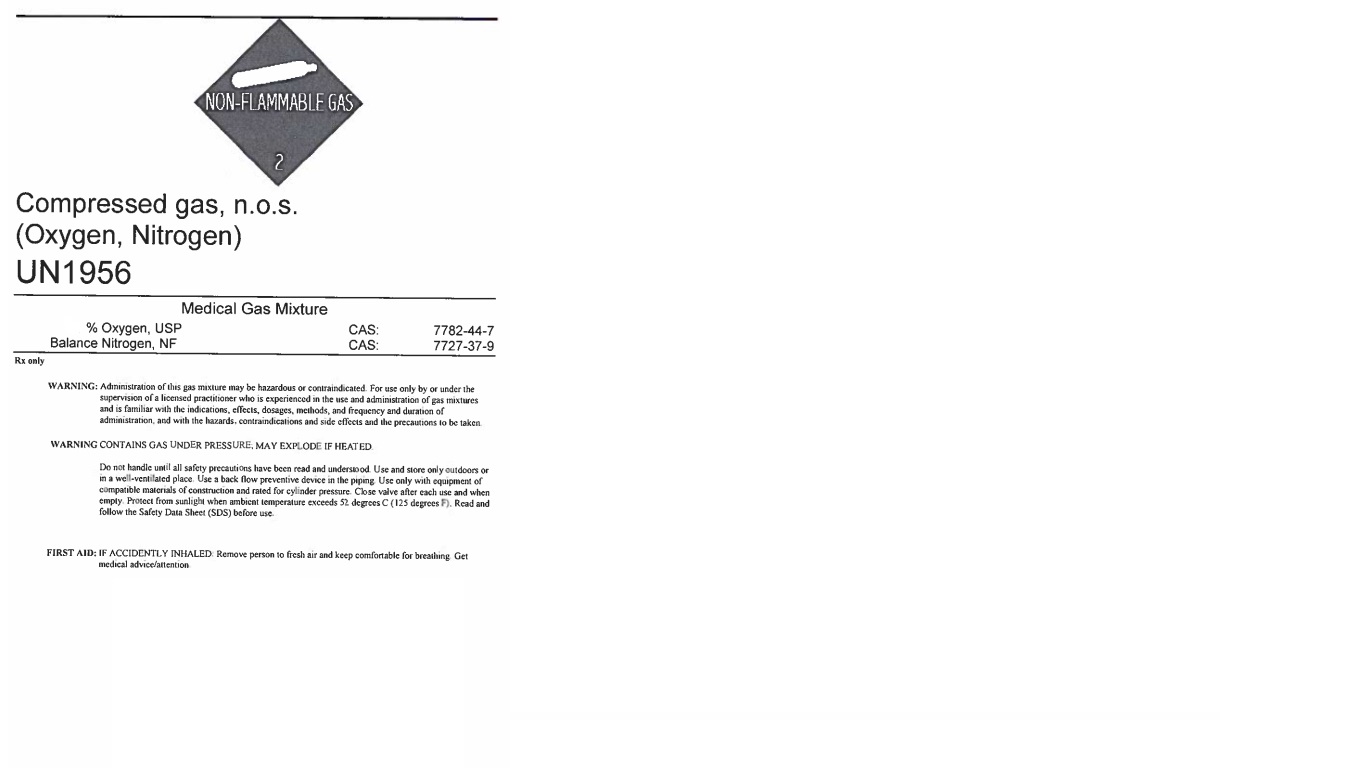 DRUG LABEL: Oxygen/Nitrogen 38/62
NDC: 55037-870 | Form: GAS
Manufacturer: MATHESON TRI-GAS, INC.
Category: prescription | Type: HUMAN PRESCRIPTION DRUG LABEL
Date: 20251202

ACTIVE INGREDIENTS: OXYGEN 380 mL/1 L
INACTIVE INGREDIENTS: NITROGEN 620 mL/1 L

Oxygen-Nitrogen 38/62

PACKAGE LABEL

Compressed gas, n.o.s.

(Oxygen, Nitrogen)

UN1956

Medical Gas Mixture

Oxygen, USP CAS: 7782-44-7

Balance Nitrogen, NF CAS: 7727-37-9

Rx only

WARNING: Administration of this gas mixture may be hazardous or contraindicated. For use only by or under the supervision of a licensed practitioner who is experienced in the use and administration of gas mixtures and is familiar with the indications, effects, dosages, methods, and frequency and duration of administration, and with the hazards, contraindications and side effects and the precautions to be taken.

WARNING CONTAINS GAS UNDER PRESSURE; MAY EXPLODE IF HEATED.

Do not handle until all safety precautions have been read and understood. Use and store only outdoors or in a well-ventilated place. Use a back flow preventive device in the piping. Use only with equipment of compatible materials of construction and rated for cylinder pressure. Close valve after each use and when empty. Protect from sunlight when ambient temperature exceeds 52 degrees C (125 degrees F). Read and follow the Safety Data Sheet (SDS) before use.

FIRST AID: IF ACCIDENTLY INHALED: Remove person to fresh air and keep comfortable for breathing. Get medical advice/attention.

DO NOT REMOVE THIS PRODUCT LABEL

Matheson

909 Lake Carolyn Pkwy

Irving, TX 75039